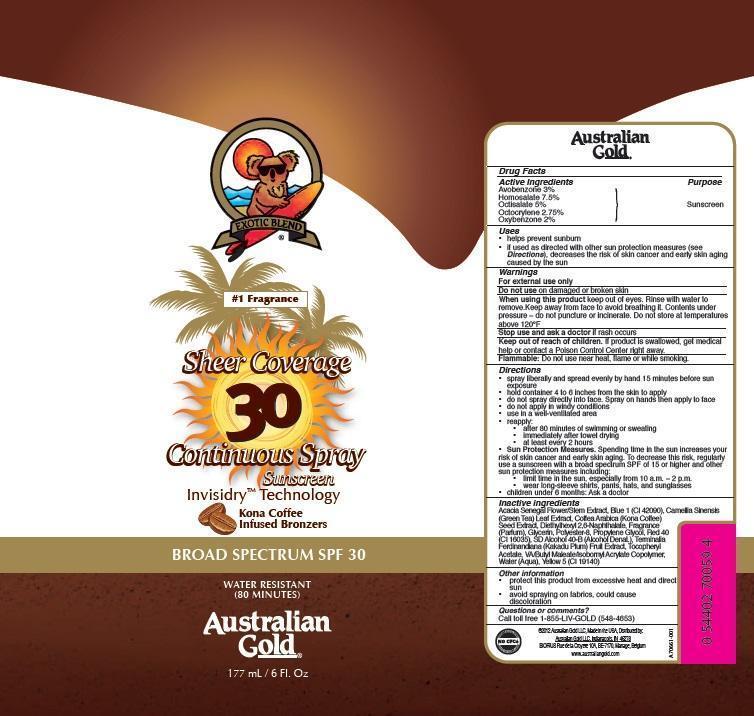 DRUG LABEL: Australian Gold
NDC: 13630-0086 | Form: AEROSOL, SPRAY
Manufacturer: Prime Packaging, Inc.
Category: otc | Type: HUMAN OTC DRUG LABEL
Date: 20200117

ACTIVE INGREDIENTS: AVOBENZONE 25.8 mg/1 mL; HOMOSALATE 64.5 mg/1 mL; OCTISALATE 43 mg/1 mL; OCTOCRYLENE 23.7 mg/1 mL; OXYBENZONE 17.2 mg/1 mL
INACTIVE INGREDIENTS: FD&C BLUE NO. 1; DIETHYLHEXYL 2,6-NAPHTHALATE; POLYESTER-8 (1400 MW, CYANODIPHENYLPROPENOYL CAPPED); FD&C RED NO. 40; DIBUTYL MALEATE; ISOBORNYL ACRYLATE; GLYCERIN; PROPYLENE GLYCOL; ACACIA SENEGAL FLOWER; KAKADU PLUM; GREEN TEA LEAF; COFFEA ARABICA SEED, ROASTED; FD&C YELLOW NO. 5; WATER

Active ingredients

Avobenzone 3%, Homosalate 7.5%, Octisalate 5%, Octocrylene 2.75%, and Oxybenzone 2 %

Purpose

Sunscreen

Uses

- helps prevent sunburn
- if used as directed with other sun protection measures (see Directions), decreases the risk of skin cancer and early skin aging caused by the sun

Warnings

OTHER SAFETY INFORMATION

For external use only

Do not use on damaged or broken skin.

When using this product keep out of eyes. Rinse with water to remove. Keep away from face to avoid breathing it. Content under pressure - do not puncture or incinerate. Do not store at temperatures above 120°F.

Stop use and ask a doctor if rash occurs.

Keep out of reach of children. If product is swallowed, get medical help or contact a Poison Control Center right away.

OTHER SAFETY INFORMATION

Flammable: Do not use near heat, flame or while smoking

Directions

- spray liberally and spread evenly by hand 15 minutes before sun exposure
- Children under 6 months: Ask a doctor
- Hold container 4 to 6 inches from the skin to apply
- Do not spray directly into face. Spray hands then apply to face.
- Do not apply in windy conditions. Use in well ventilated areas.
- reapply:
- after 80 minutes of swimming or sweating
- immediately after towel drying
- at least every 2 hours

Inactive Ingredients

Acacia Senegal Flower/Stem Extract, Blue 1 (Cl 42090), Camellia Sinensis (Green Tea) Leaf Extract, Coddea Arabica (Kona Coffee) Seed Extract, Diethylhexyl 2,6-Naphthalate, Fragrance (Parfum), Glycerin, Polyester-8, Propylene Glycol, Red-40 (Cl 16035), SD Alcohol 40-B (Alcohol Denat), Terminalia Ferdinandiana (Kakadu Plum) Fruit Extract, TocopherylAcetate, VA/Butyl Maleate/Isobomyl Acrylate Copolymer, Water (Aqua), Yellow 5 (Cl 19140)

Other information

- protect this product from excesive heat and direct sun
- avoid spraying on fabrics, could cause discoloration

Questions or Comments?

Call toll free 1-800-LIV-GOLD (548-4653)

PRINCIPAL DISPLAY PANEL - 177 mL Can Label

Exotic Blend

#1 Fragrance

Sheer Coverage

30

Continuous Spray

Sunscreen

Invisidry™ Technology

Kona Coffee

Infused Bronzers

Broad Spectrum SPF 30

Water Resistant

(80 Minutes)

Autralian

G old®

177 mL / 6Fl. Oz